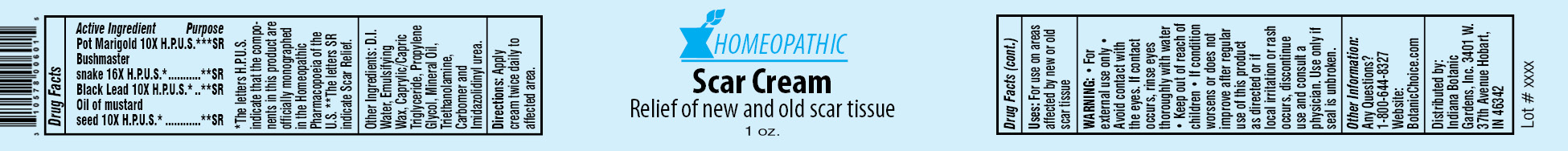 DRUG LABEL: Homeopathic Scar
NDC: 10578-006 | Form: CREAM
Manufacturer: Indiana Botanic Gardens
Category: homeopathic | Type: HUMAN OTC DRUG LABEL
Date: 20120427

ACTIVE INGREDIENTS: CALENDULA OFFICINALIS FLOWER 10 [hp_X]/28 g; LACHESIS MUTA VENOM 16 [hp_X]/28 g; GRAPHITE 10 [hp_X]/28 g; ALLYLTHIOUREA 10 [hp_X]/28 g
INACTIVE INGREDIENTS: WATER; CETOSTEARYL ALCOHOL; POLYSORBATE 60; TRICAPRYLIN; PROPYLENE GLYCOL; MINERAL OIL; TROLAMINE; CARBOMER 934; IMIDUREA

Homeopathic Scar Cream

Active Ingredients

Pot Marigold 10X H.P.U.S.*

Bushmaster snake 16X H.P.U.S.*

Black Lead 10X H.P.U.S.*

Oil of mustard seed 10X H.P.U.S.*

Purpose

**SR

**SR

**SR

**SR

*The letters H.P.U.S. indicate that the components in this product are officially monographed in the Homeopathic Pharmacopoeia of the U.S. **The letters SR indicate Scar Relief.

Other Ingredients:

D.I. Water, Emulsifying Wax, Caprylic/Capric Triglyceride, Propylene Glycol, Mineral Oil, Triethanolamine, Carbomer and Imidazolidinyl urea.

Directions:

Apply cream twice daily to affected area.

Uses:

For use on areas affected by new or old scar tissue

WARNING:

- for external use only
- Avoid contact with the eyes. If contact occurs, rinse eyes thoroughly with water

- Keep out of reach of children

STOP USE

- If condition worsens or does not improve after regular use of this product as directed or if local irritation or rash occurs, discontinue use and consult a physician.

Use only if seal is unbroken.

Other Information:

Any Questions?

1-800-644-8327

Website:

BotanicChoice.com

Distributed by:

Indiana Botanic Gardens, Inc. 3401 W. 37th Avenue Hobart, IN 46342

Homeopathic Scar Cream

Relief of new and old scar tissue

1 oz.